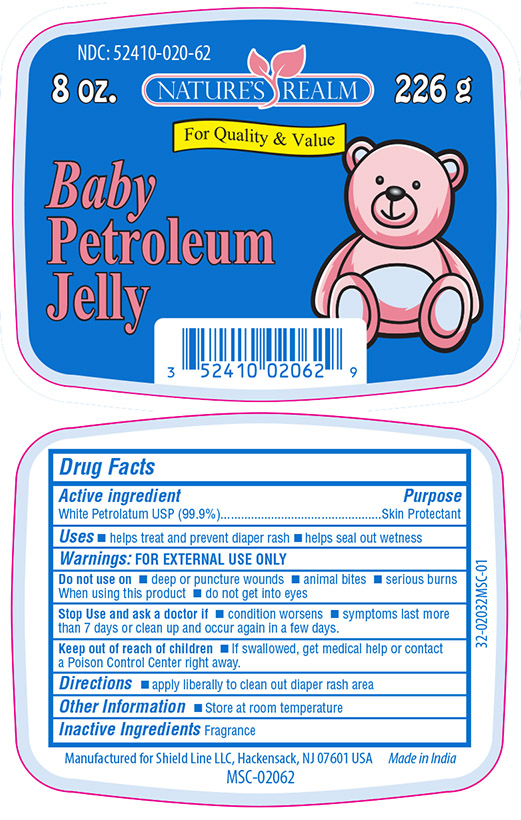 DRUG LABEL: Baby Petrolatum Jelly
NDC: 52410-0206 | Form: JELLY
Manufacturer: SHIELD LINE LLC
Category: otc | Type: HUMAN OTC DRUG LABEL
Date: 20250815

ACTIVE INGREDIENTS: PETROLATUM 99.9 g/100 g
INACTIVE INGREDIENTS: WATER

Active Ingredient

White Petrolatum USP (99.9%)

Purpose

Skin Protectant

Uses

- helps treat and prevent diaper rash
- helps seal out wetness

Warnings: FOR EXTERNAL USE ONLY

Do not use on

- deep and punture wounds
- animal bites
- serious burns

When using this product

- do not get into eyes

Stop Use and ask a doctor if

- condition worsens
- symptoms last more than 7 days or clean up and occur again in few days

Keep out of reach of children

- if swallowed, get medical help or contact a Poison Control Center right away

Directions

- apply liberally to clean out diaper rash area

Other Information

- Store at room temperature

Inactive Ingredient

Fragrance